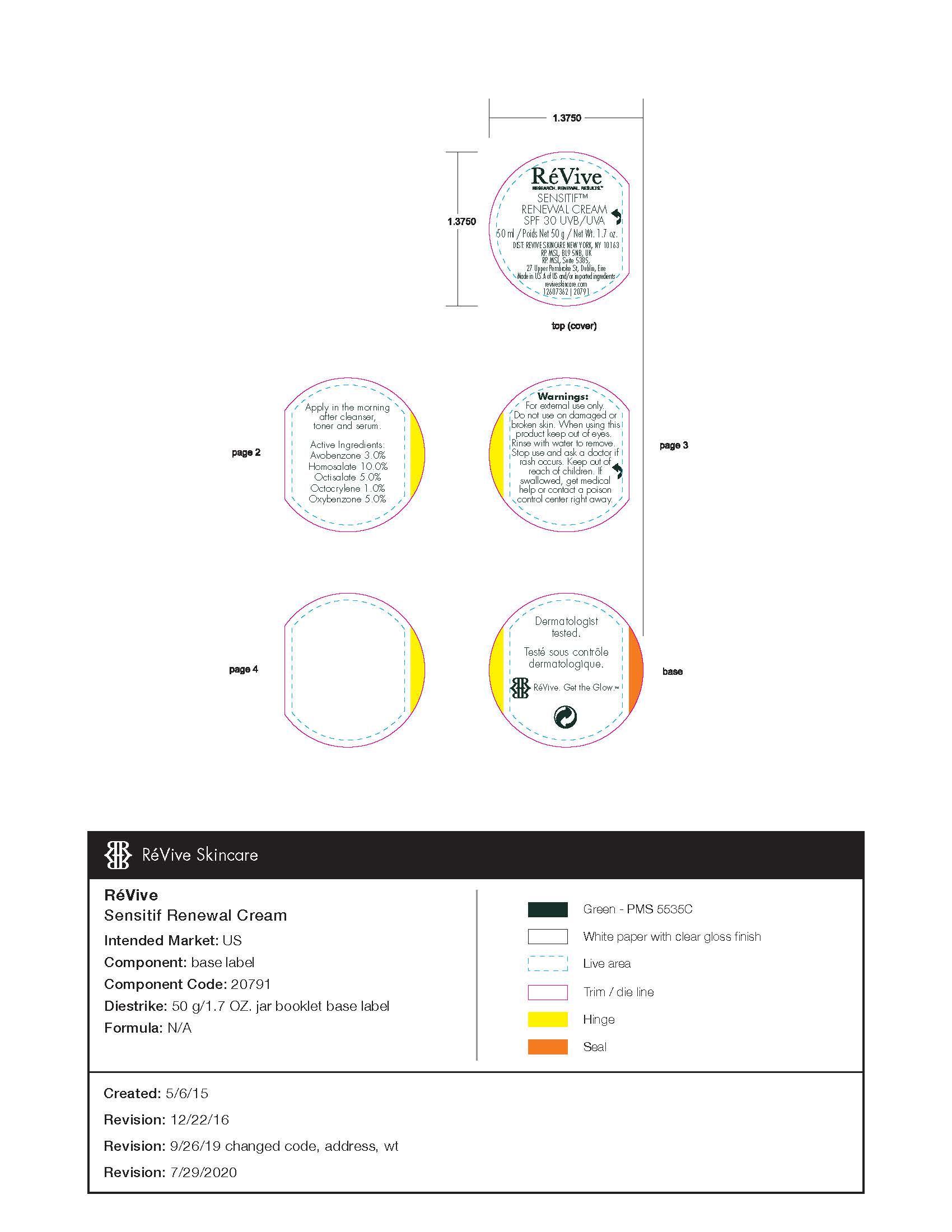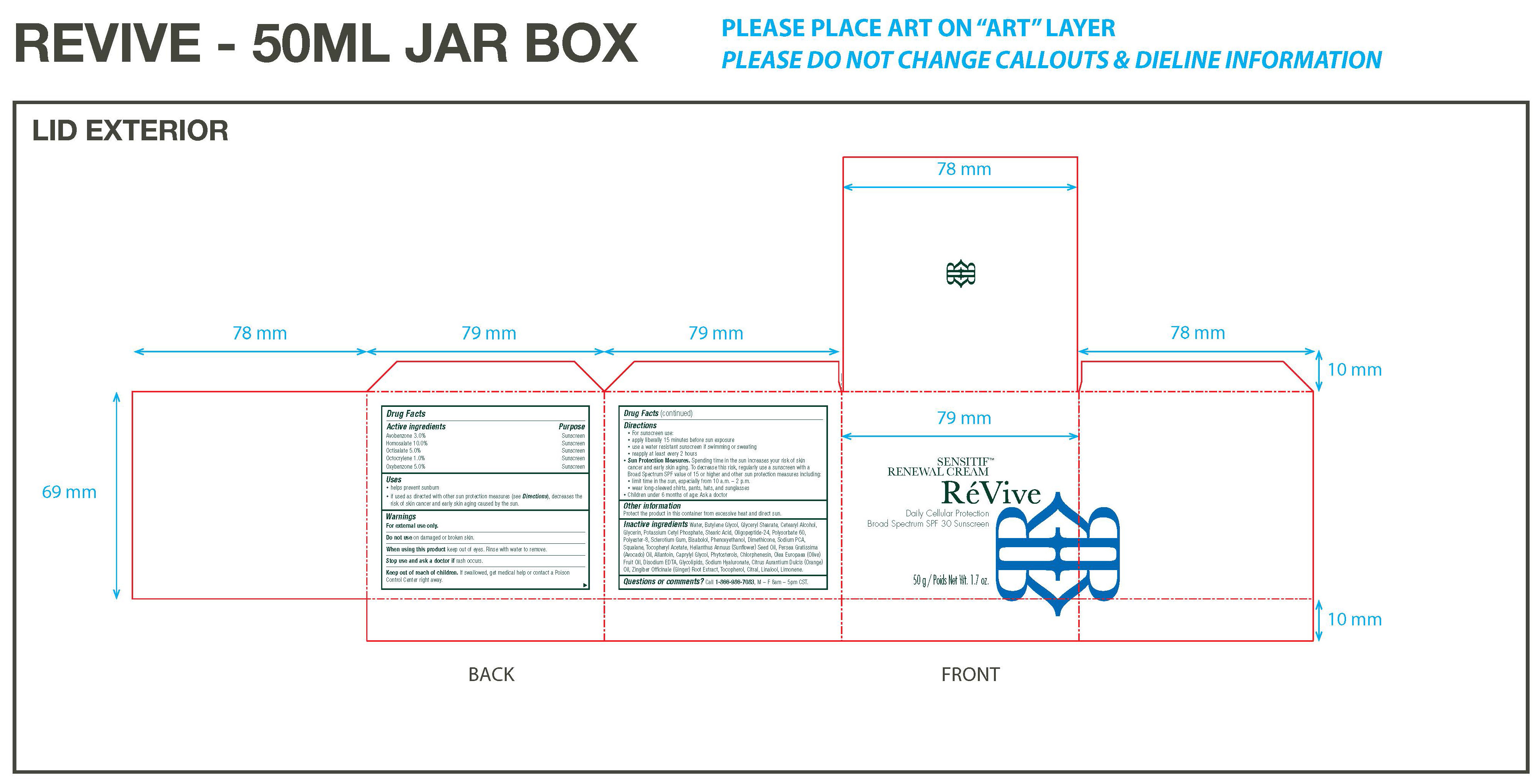 DRUG LABEL: MOISTURIZER
NDC: 61354-035 | Form: CREAM
Manufacturer: Oxygen Development LLC
Category: otc | Type: HUMAN OTC DRUG LABEL
Date: 20230210

ACTIVE INGREDIENTS: HOMOSALATE 10 mg/100 mg; OXYBENZONE 5 mg/100 mg; OCTISALATE 5 mg/100 mg; AVOBENZONE 3 mg/100 mg; OCTOCRYLENE 1 mg/100 mg
INACTIVE INGREDIENTS: CETOSTEARYL ALCOHOL; DIMETHICONE; SQUALANE; STEARIC ACID; .ALPHA.-BISABOLOL, (+/-)-; SUNFLOWER OIL; POLYSORBATE 60; BETASIZOFIRAN; PHENOXYETHANOL; ALPHA-TOCOPHEROL ACETATE; WATER; POTASSIUM CETYL PHOSPHATE; GLYCERIN; POLYESTER-8 (1400 MW, CYANODIPHENYLPROPENOYL CAPPED); BUTYLENE GLYCOL; GLYCERYL MONOSTEARATE

Revive Sensitif Renewal Cream Daily cellular protection broad spectrum SPF 30 sunscreen 50g

Active ingredients

Avobenzone 3%

Homosalate 10%

Octisalate 5%

Octcrylene 1%

Oxygenzone 5%

Purpose: Sunscreen

Purpose

Sunscreen

Uses

- helps prevent sunburn
- if used as directed with other sun protection measures, decreases the risk of skin cancer and early skin aging caused by the sun

Warnings

For external use only

Do not use

on damaged or broken skin

When using

this product keep out of eyes. Rinse with water to remove.

Stop Use

and ask a doctor if rash occurs

Keep out of reach of children

If swallowed, get medical help or contact a poison control center right away

Directions

- For sunscreen use:
- apply liberally 15 minutes before sun exposure
- use a water resistant sunscreen if swimming or sweating
- reapply at least every 2 hours

Sun Protection Measures

Spending time in the sun increased your risk of skin cancer and early skin aging. To decrease this risk, regularly use a sunscreen with a Broad Spectrum SPF valuye of 15 or higher and other sun protection measures inclusing:

- limit time in the sun, specially from 10am - 2pm
- children under 6 months of age: ask a doctor

other information

Protect the product in this container from excessive heat and direct sun

Inactive ingredients

water, butylene glycol, glyceryl stearate, cetearyl alcohol, glycerin, potassium cetyl phosphate, stearic acid, oligopeptide-24, polysorbate 60, polyester-8, sclerotium gum, bisabolol, phenoxyethanol, dimethicone, sodium PCA, squalana, tocopheryl acetate, helianthus annus (sunflower) seed oil, persea gratissima (avocado) oil, allantoin, caprylyl glycol, phytosterols, chlorphenesin, olea europaea (olive) fruit oil, disodium EDTA, glycolipids, sodium hyaluronate, citrus aurantium dulcis (orange) oil, zingiber officinale (ginger) root extract, tocopherol, citral, linalool, limonene